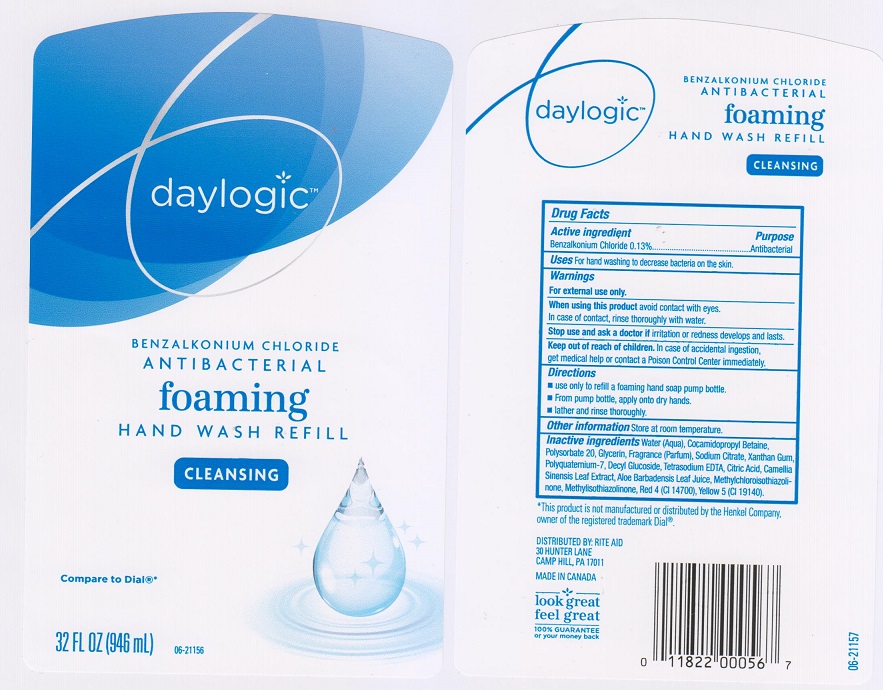 DRUG LABEL: Daylogic Antibacterial Foaming Wash Refill
NDC: 11822-1243 | Form: LIQUID
Manufacturer: Rite Aid Corporation
Category: otc | Type: HUMAN OTC DRUG LABEL
Date: 20161021

ACTIVE INGREDIENTS: BENZALKONIUM CHLORIDE 1.3 mg/1 mL
INACTIVE INGREDIENTS: WATER; COCAMIDOPROPYL BETAINE; POLYSORBATE 20; GLYCERIN; SODIUM CITRATE; XANTHAN GUM; POLYQUATERNIUM-7 (70/30 ACRYLAMIDE/DADMAC; 1600000 MW); DECYL GLUCOSIDE; EDETATE SODIUM; CITRIC ACID MONOHYDRATE; GREEN TEA LEAF; ALOE VERA LEAF; METHYLCHLOROISOTHIAZOLINONE; METHYLISOTHIAZOLINONE; FD&C RED NO. 4; FD&C YELLOW NO. 5

Drug Facts

Active ingredient

Benzalkonium chloride 0.13%

Purpose

Antibacterial

Uses

For hand washing to decrease bacteria on the skin.

Warnings

For external use only.

When using this product

avoid contact with eyes. In case of contact, rinse thoroughly with water.

Stop use and ask a doctor if

irritation or redness develops and lasts.

Keep out of reach of children.

In case of accidental ingestion, get medical help or contact a Poison Control Center immediately.

Directions

- use only to refill a foaming hand soap pump bottle.
- from pump bottle, apply onto dry hands.
- lather and rinse thoroughly.

Other information

store at room temperature.

Inactive ingredients

Water (Aqua), Cocamidopropyl Betaine, Polysorbate 20, Glycerin, Fragrance (Parfum), Sodium Citrate, Xanthan Gum, Polyquaternium-7, Decyl Glucoside, Tetrasodium EDTA, Citric Acid, Camellia Sinensis Leaf Extract, Aloe Barbadensis Leaf Juice, Methylchloroisothiazolinone, Methylisothiazolinone, Red 4 (CI 14700), Yellow 5 (CI 19140).